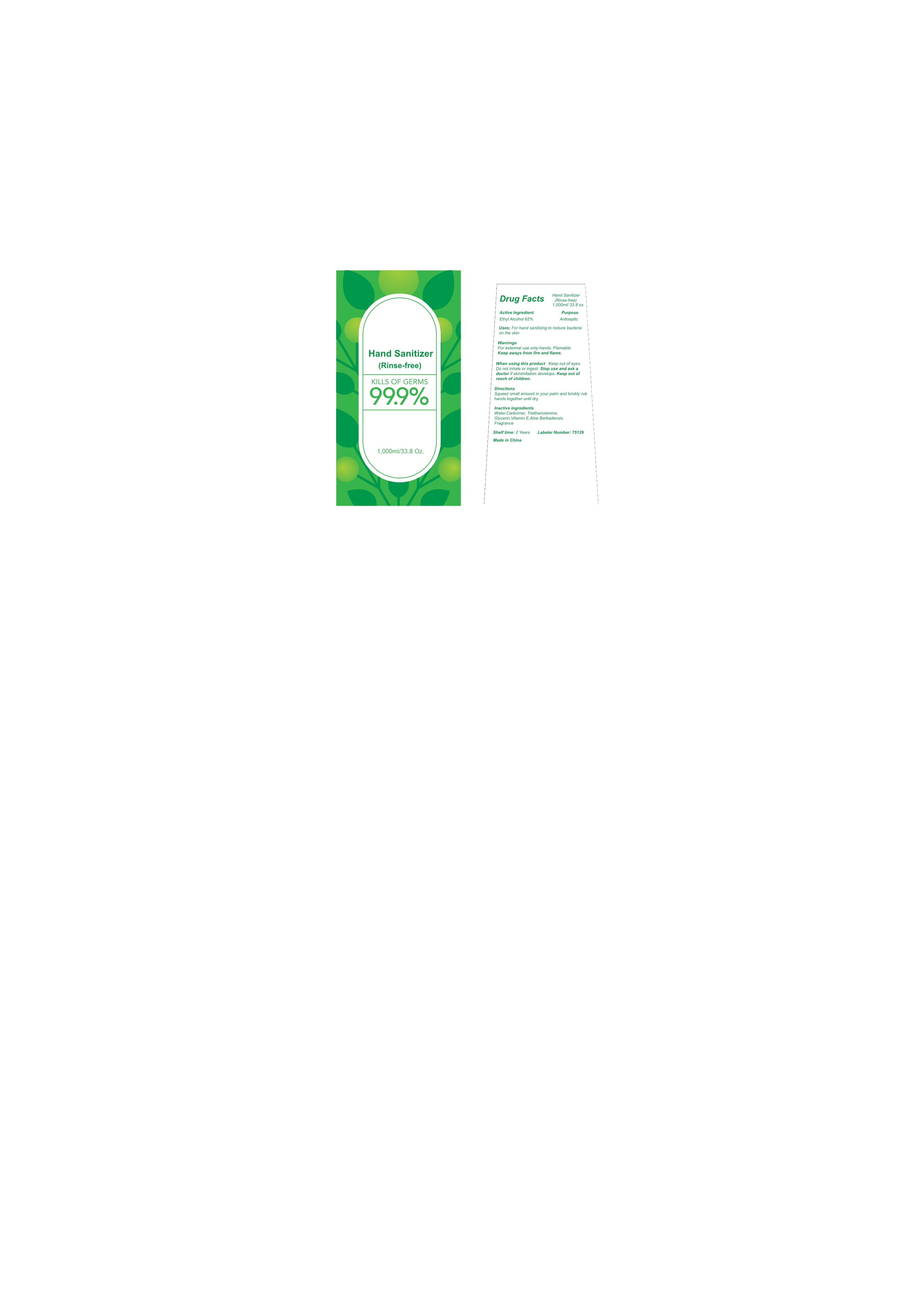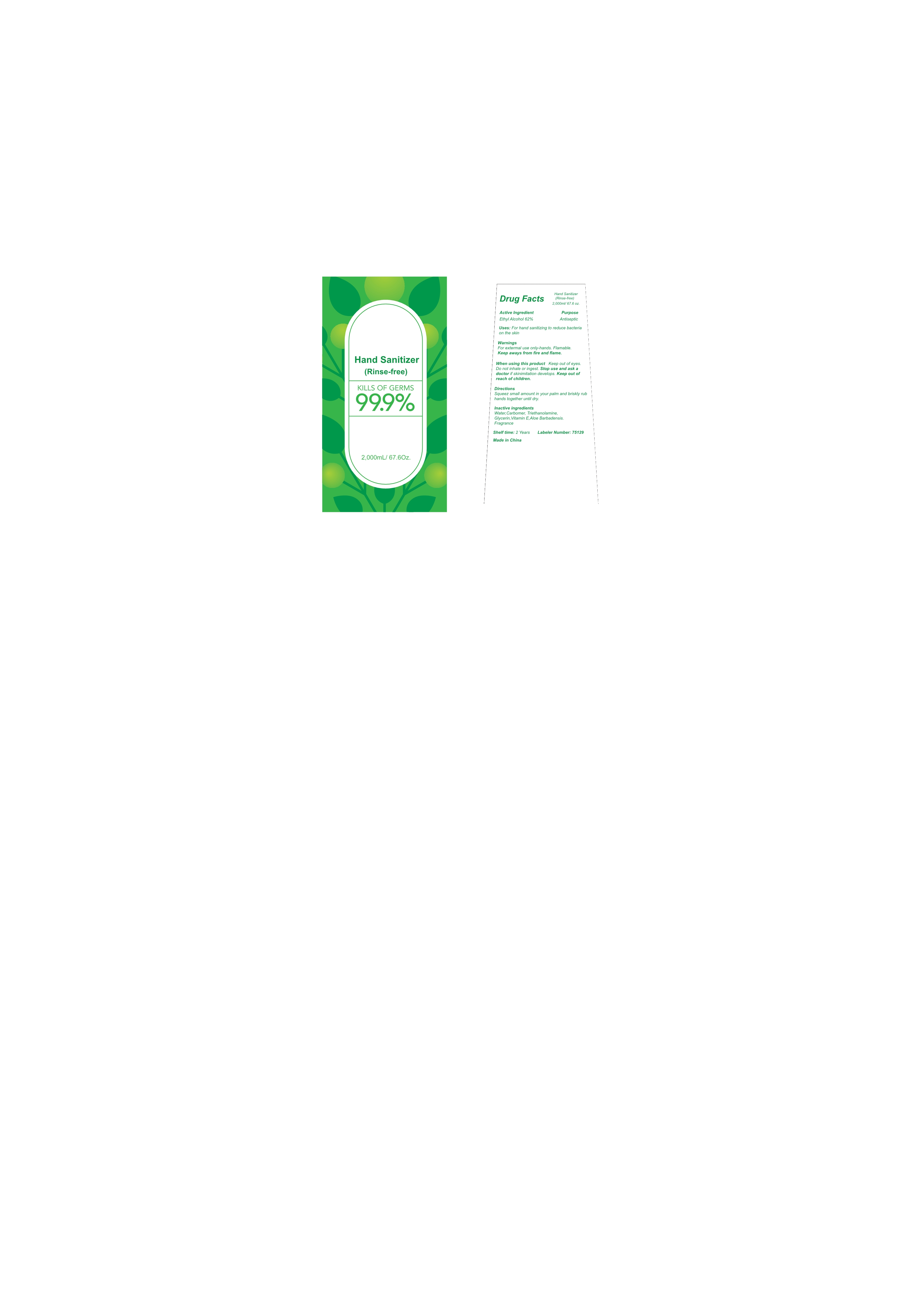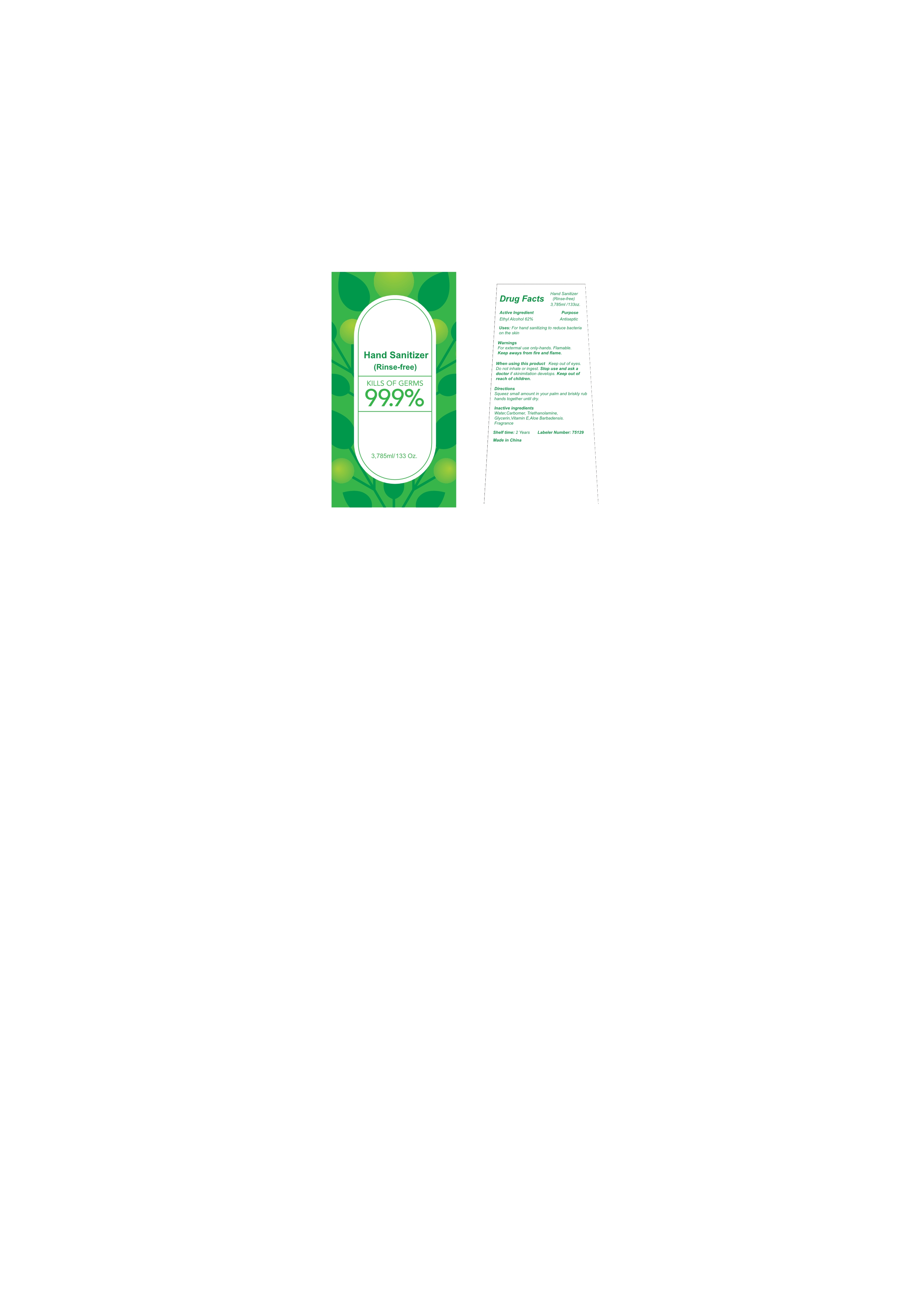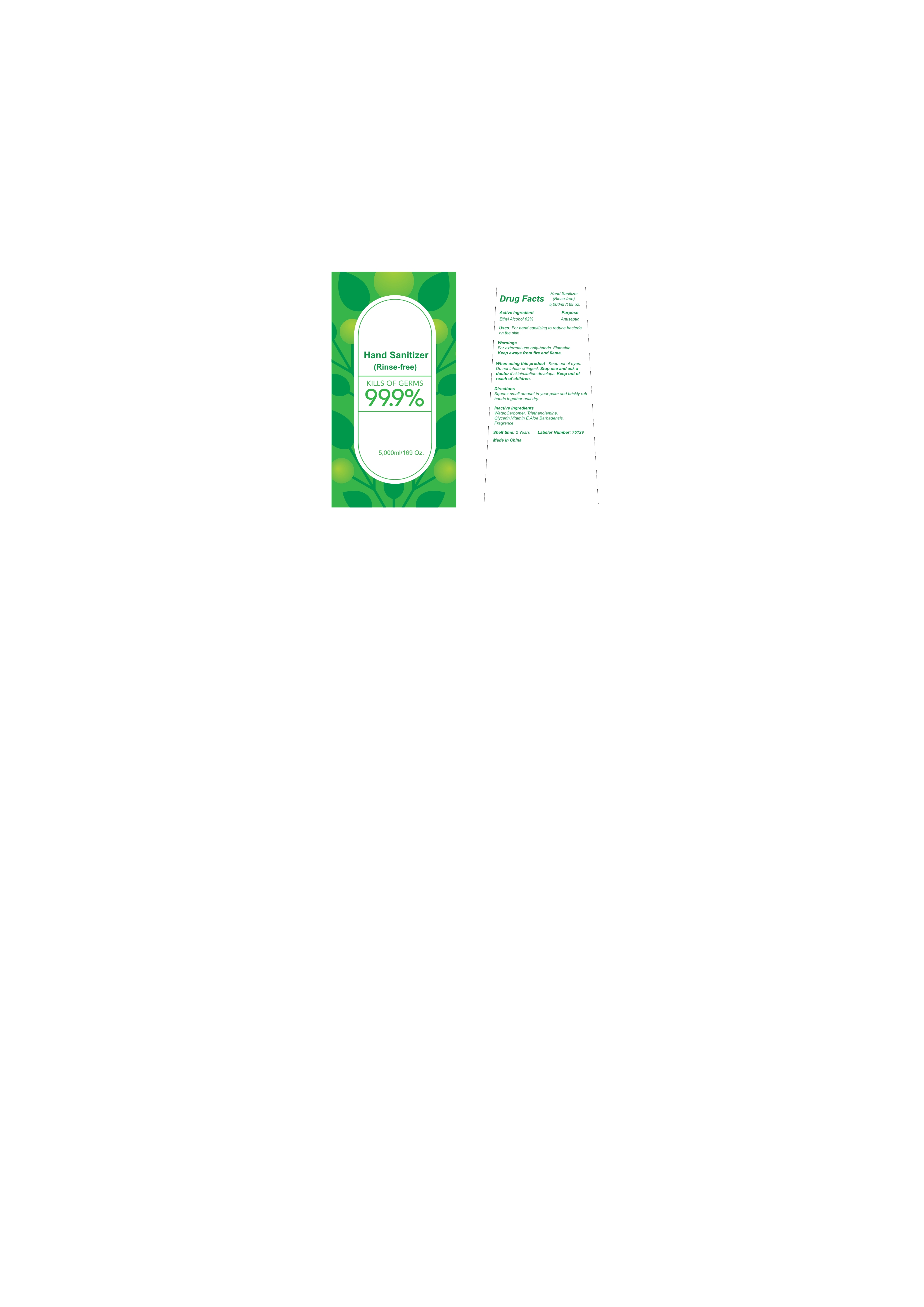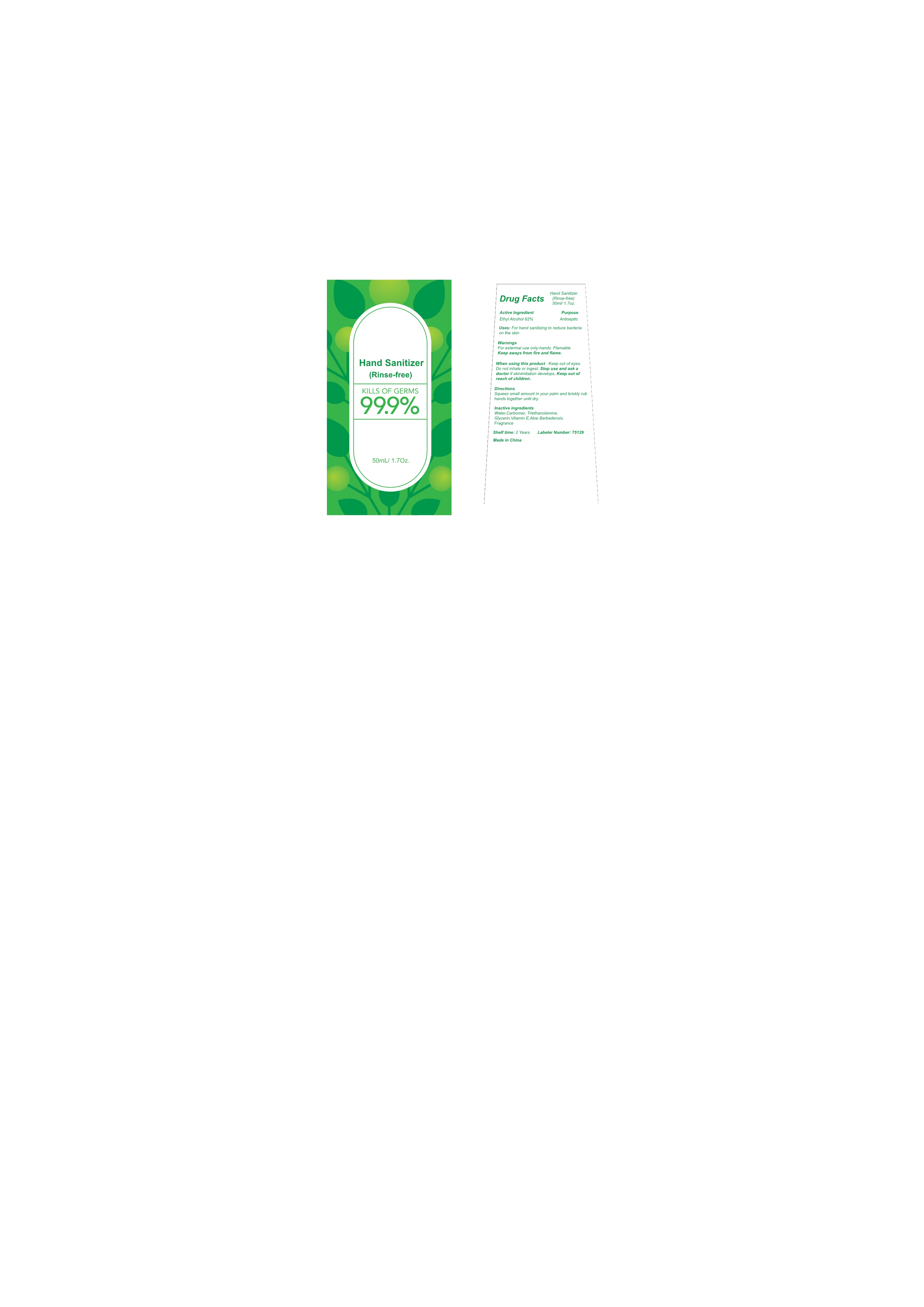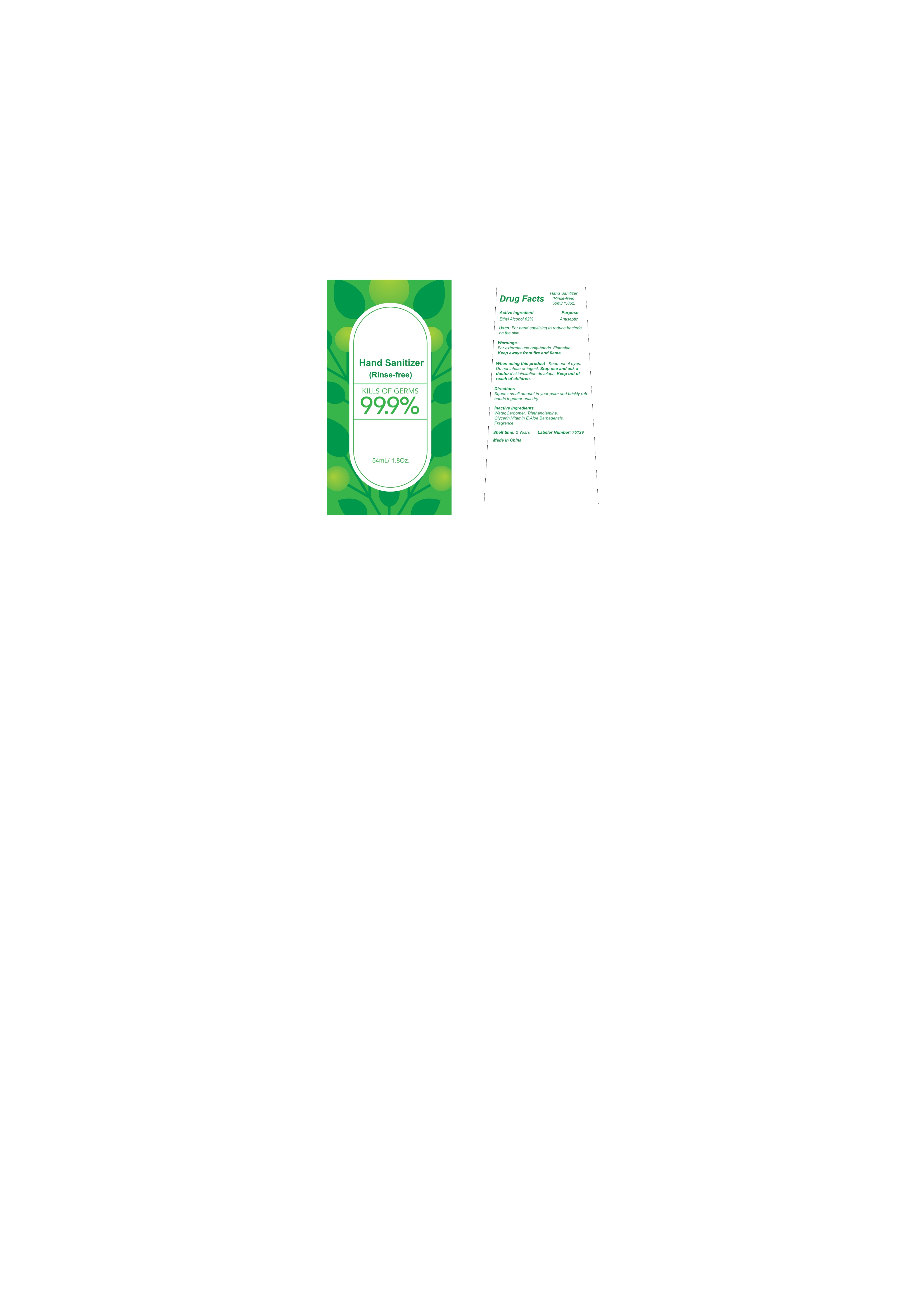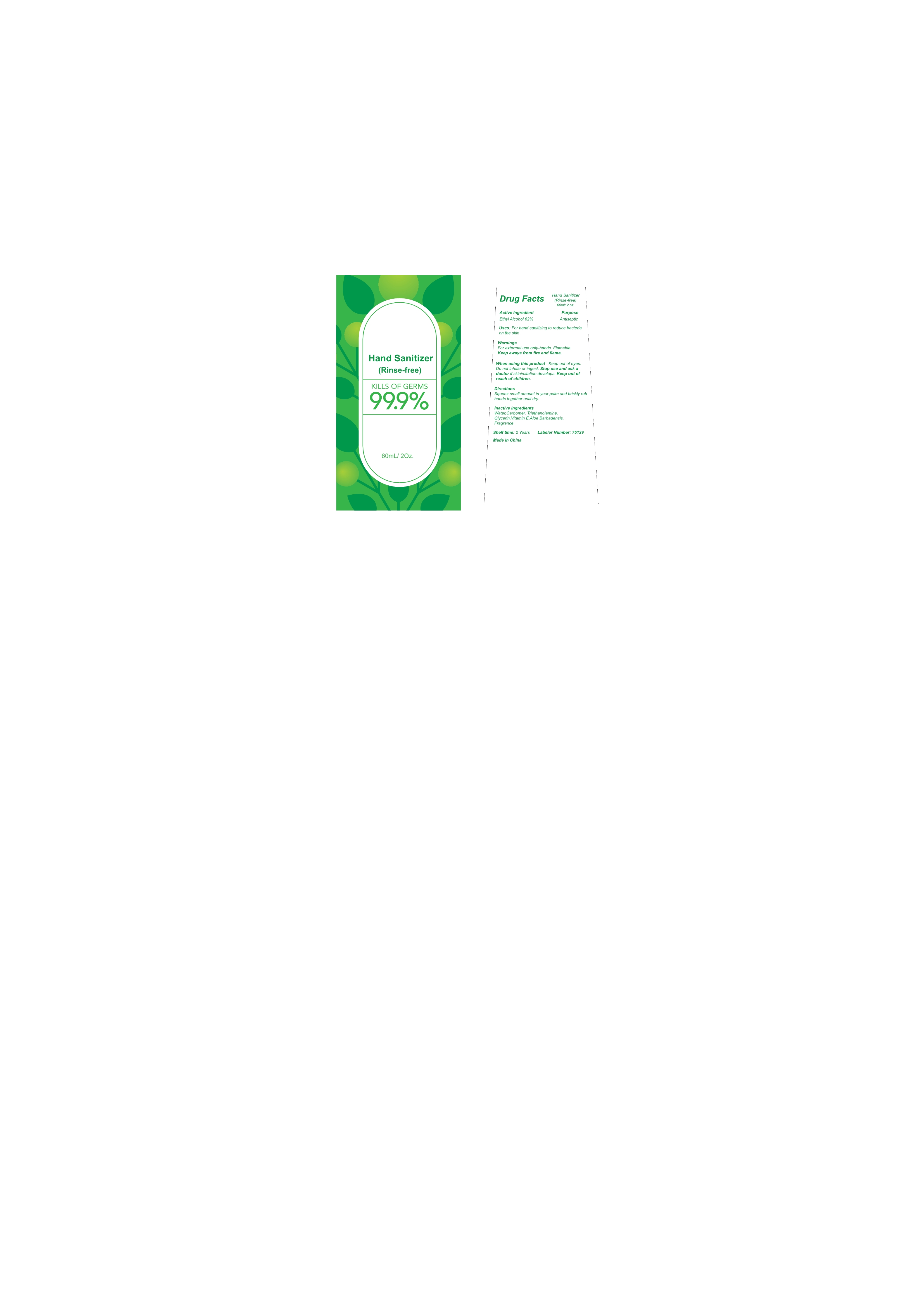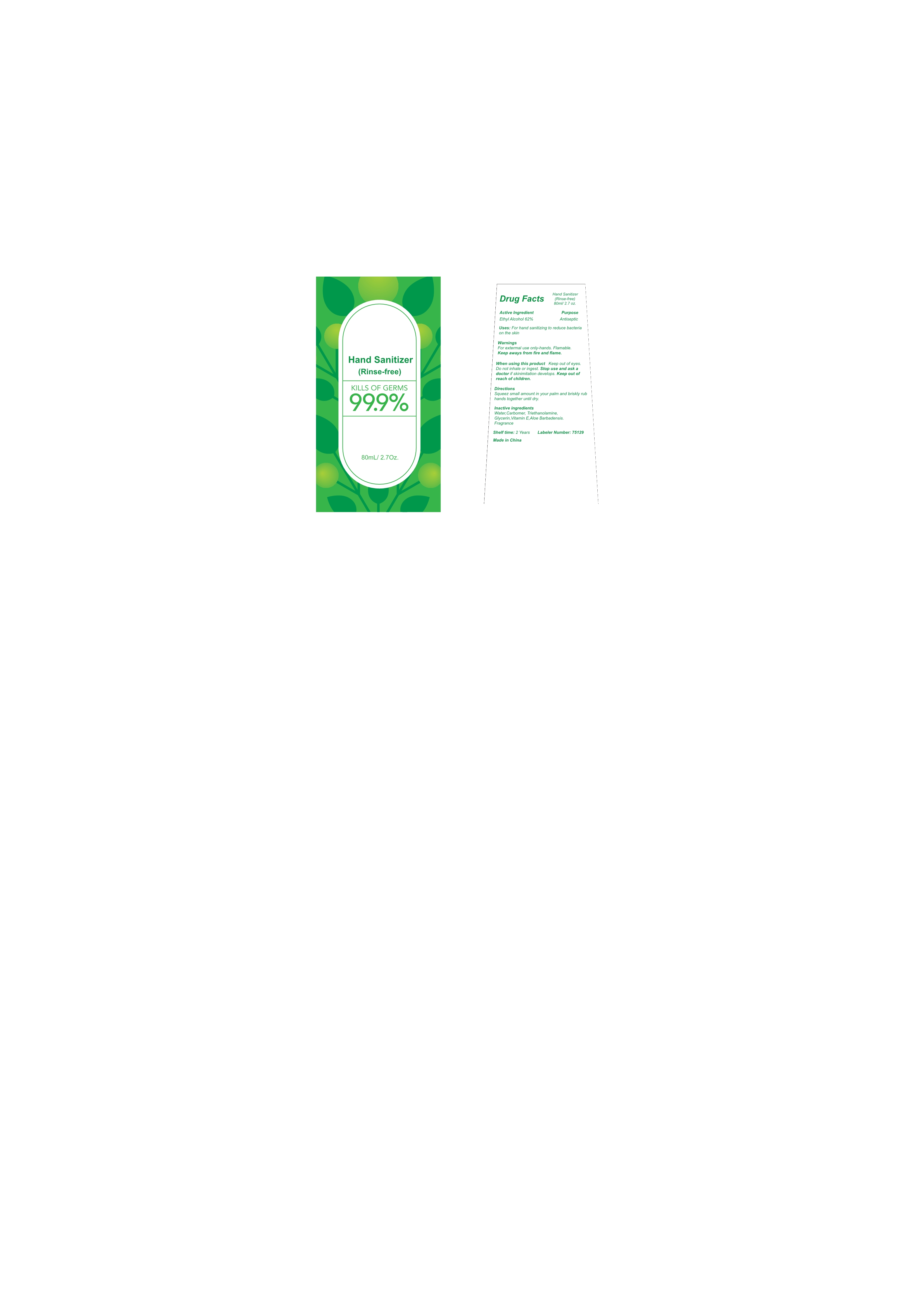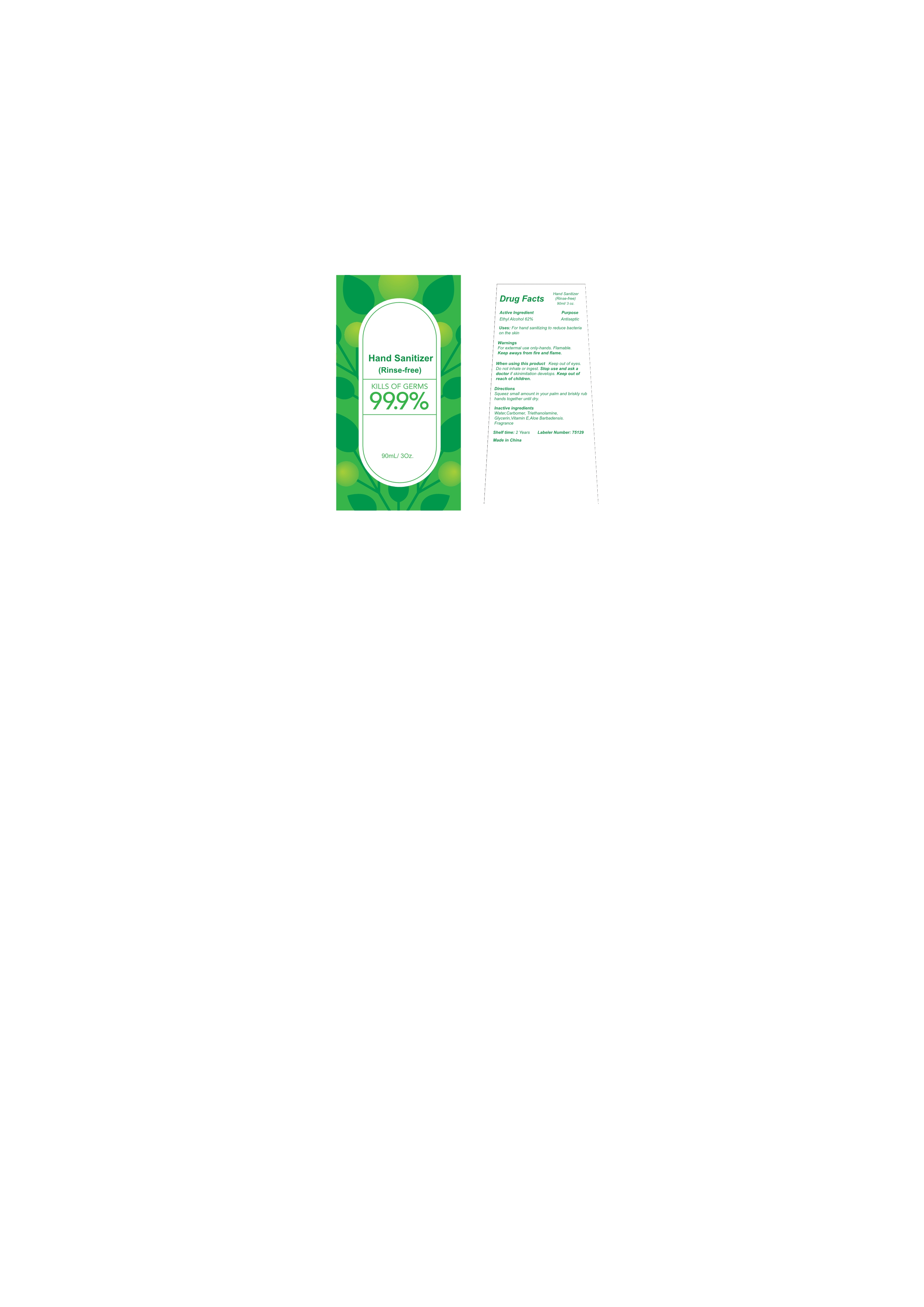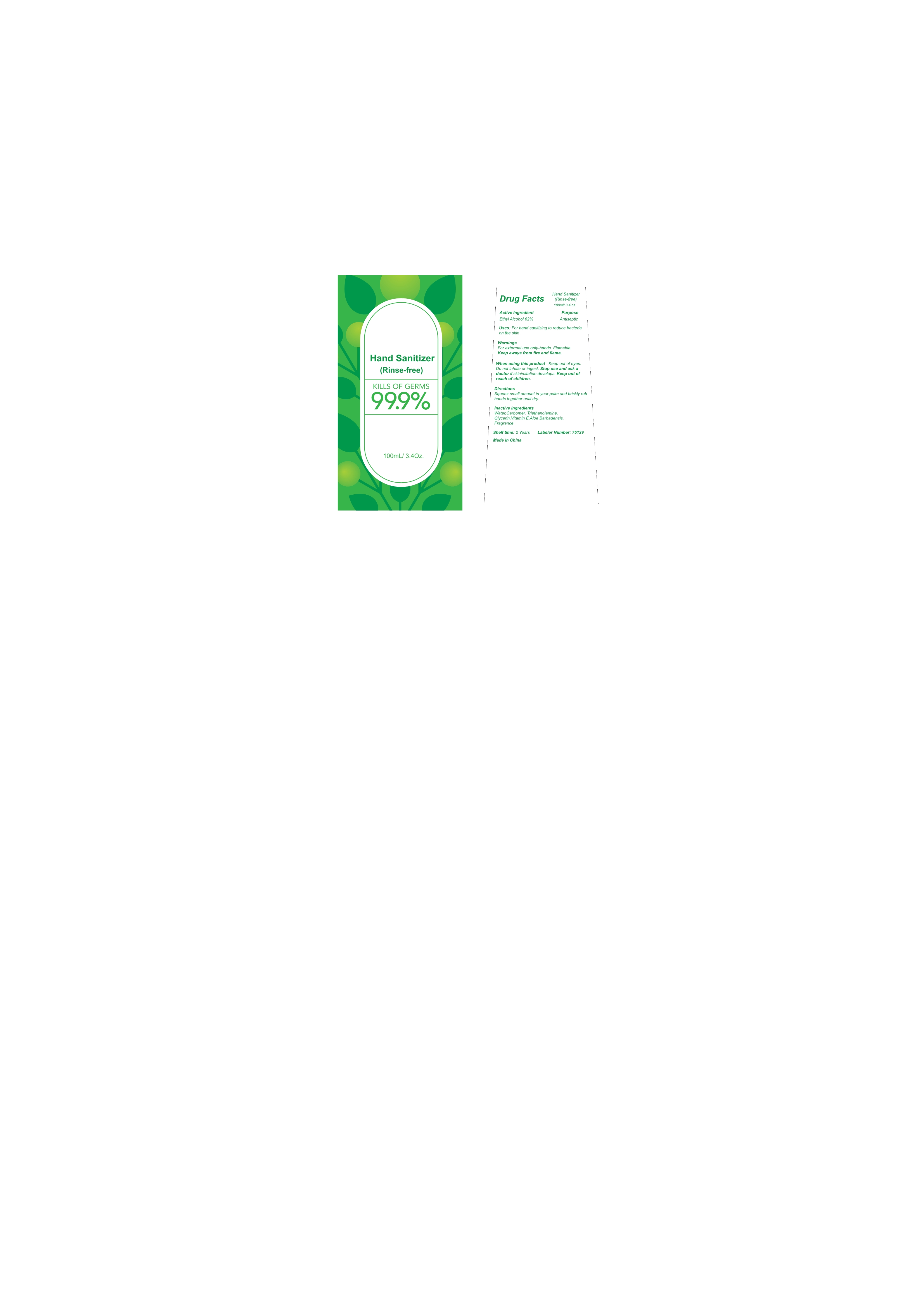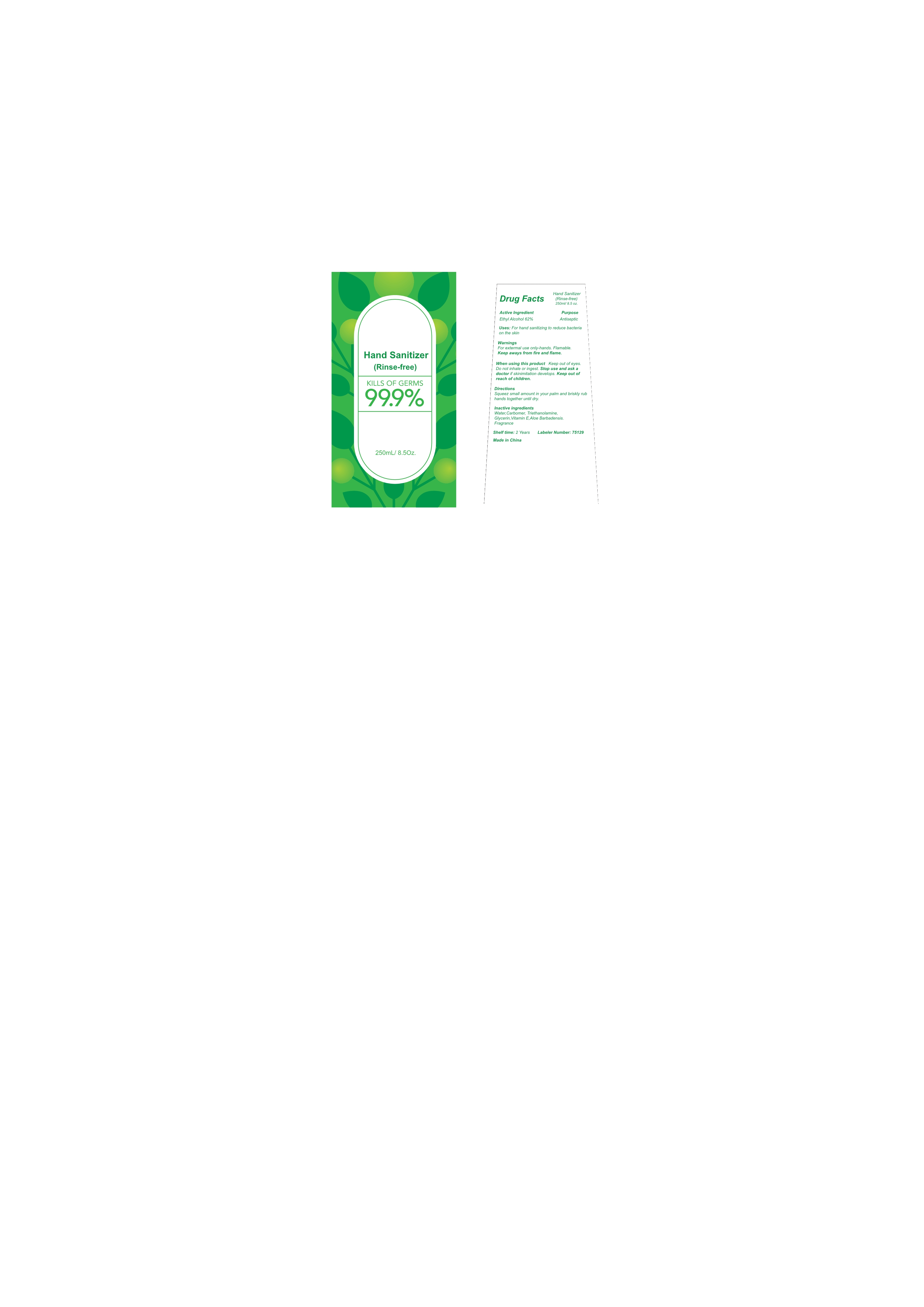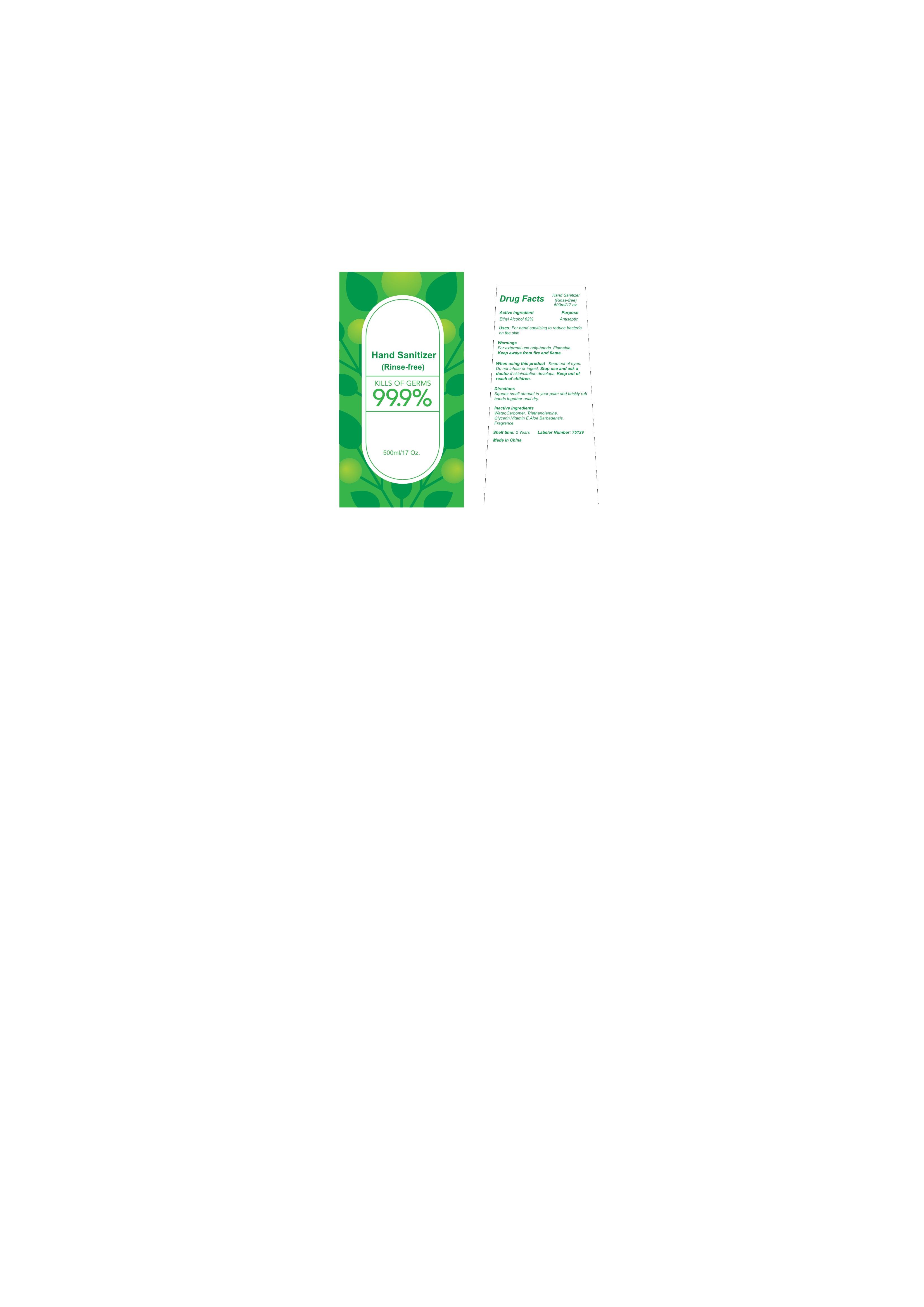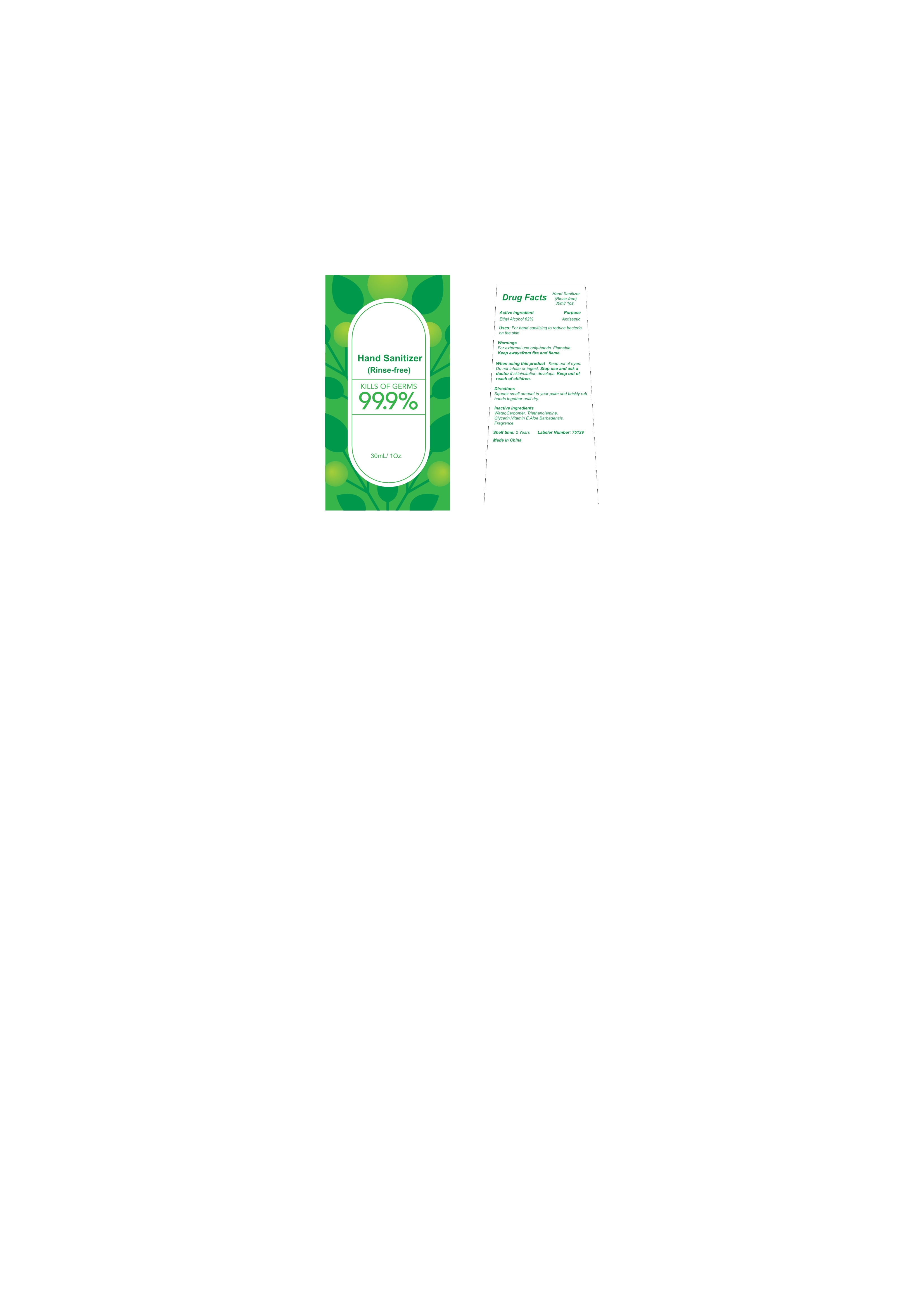 DRUG LABEL: Hand Sanitizer (Rinse-free)
NDC: 75129-001 | Form: GEL
Manufacturer: Shanghai Rayshine ENVI-TECH Developing CO., Ltd.
Category: otc | Type: HUMAN OTC DRUG LABEL
Date: 20200517

ACTIVE INGREDIENTS: ALCOHOL 62 mL/100 mL
INACTIVE INGREDIENTS: CARBOMER HOMOPOLYMER, UNSPECIFIED TYPE; TROLAMINE; GLYCERIN; WATER

Hand Sanitizer (Rinse-free)

Active Ingredient

Ethyl Alcohol 62%

Purpose

Antiseptic

Uses

For hand sanitizing to reduce bacteria
on the skin.

Warnings

For extermal use only-hands. Flamable.Keep awaysfrom fire and flame.

When using this product

Keep out of eyes.Do not inhale or ingest. Stop use and ask a doctor if skinimitation develops. Keep out of reach of children.

Directions

Squeez small amount in your palm and briskly rub hands together until dry.

Inactive ingredients

Water,Carbomer,Triethanolamine,Glycerin,Vitamin E,Aloe Barbadensis.Fragrance.